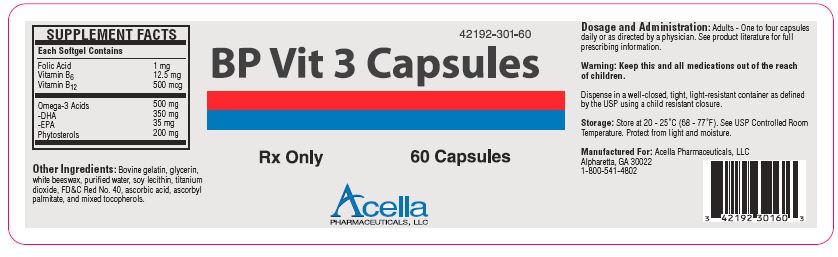 DRUG LABEL: BP Vit 3 
NDC: 42192-301 | Form: CAPSULE, COATED
Manufacturer: Acella Pharmaceuticals, LLC
Category: prescription | Type: HUMAN PRESCRIPTION DRUG LABEL
Date: 20250213

ACTIVE INGREDIENTS: FOLIC ACID 1 mg/1 1; PYRIDOXINE HYDROCHLORIDE 12.5 mg/1 1; CYANOCOBALAMIN 500 ug/1 1; OMEGA-3 FATTY ACIDS 500 mg/1 1; DOCONEXENT 350 mg/1 1; ICOSAPENT 35 mg/1 1; .BETA.-SITOSTEROL 200 mg/1 1
INACTIVE INGREDIENTS: GELATIN; GLYCERIN; WHITE WAX; WATER; LECITHIN, SOYBEAN; TITANIUM DIOXIDE; FD&C RED NO. 40; ASCORBIC ACID; ASCORBYL PALMITATE; TOCOPHEROL

BP Vit 3 Capsules
Rx Only

STATEMENT OF IDENTITY: BP Vit 3 is a prescription improving nutritional status in conditions requiring Essential Fatty Acid, Vitamin B12 and B6 and Folic Acid supplementation capsule. Each capsule is imprinted with “BP 301” on one side.

WARNINGS

WARNING: Folic Acid in doses above 0.1 mg daily may obscure pernicious anemia in that hematological remission can occur while neurological manifestations remain progressive.

Keep this and all medications out of the reach of children.

DOSAGE AND ADMINISTRATION: Adults: One to four capsules as directed by a physician.

SUPPLEMENT FACTS
Each Capsule Contains
Folic Acid | 1 mg
Vitamin B6 | 12.5 mg
Vitamin B12 | 500 mcg
Omega-3 Acids | 500 mg
-DHA | 350 mg
-EPA | 35 mg
Phytosterols | 200 mg

How Supplied: BP Vit 3 Capsules are supplied as red, opaque, oblong, imprinted capsules. Each capsule is imprinted with “BP 301” on one side. BP Vit 3 capsules are available in bottles of 60 (42192-301-60).

The listed product number is not a National Drug Code, but has merely been formatted to comply with industry practice standard for pharmacy and insurance computer systems.

OTHER INGREDIENTS: bovine gelatin, glycerin, white beeswax, purified water, soy lecithin, titanium dioxide, FD&C Red #40, ascorbic acid, ascorbyl palmitate and mixed tocopherols.

PRECAUTIONS

PRECAUTIONS: Folic Acid in doses above 0.1 mg daily may obscure pernicious anemia in that hematological remission can occur while neurological manifestations remain progressive.

SAFE HANDLING WARNING

STORAGE: Store at 20° - 25°C (68° - 77°F); excursions permitted to 15° - 30°C (59° - 86°F) [See USP Controlled Room Temperature.]

HEALTH CLAIM

HEALTH CLAIMS: These statements have not been evaluated by the Food and Drug Administration. This product is not intended to diagnose, treat, cure or prevent any disease.

PACKAGE LABEL.PRINCIPAL DISPLAY PANEL - 60 capsule container image

42192-301-60

BP Vit 3 Capsules

Rx Only 60 Capsules

Acella
PHARMACUETICALS, LLC